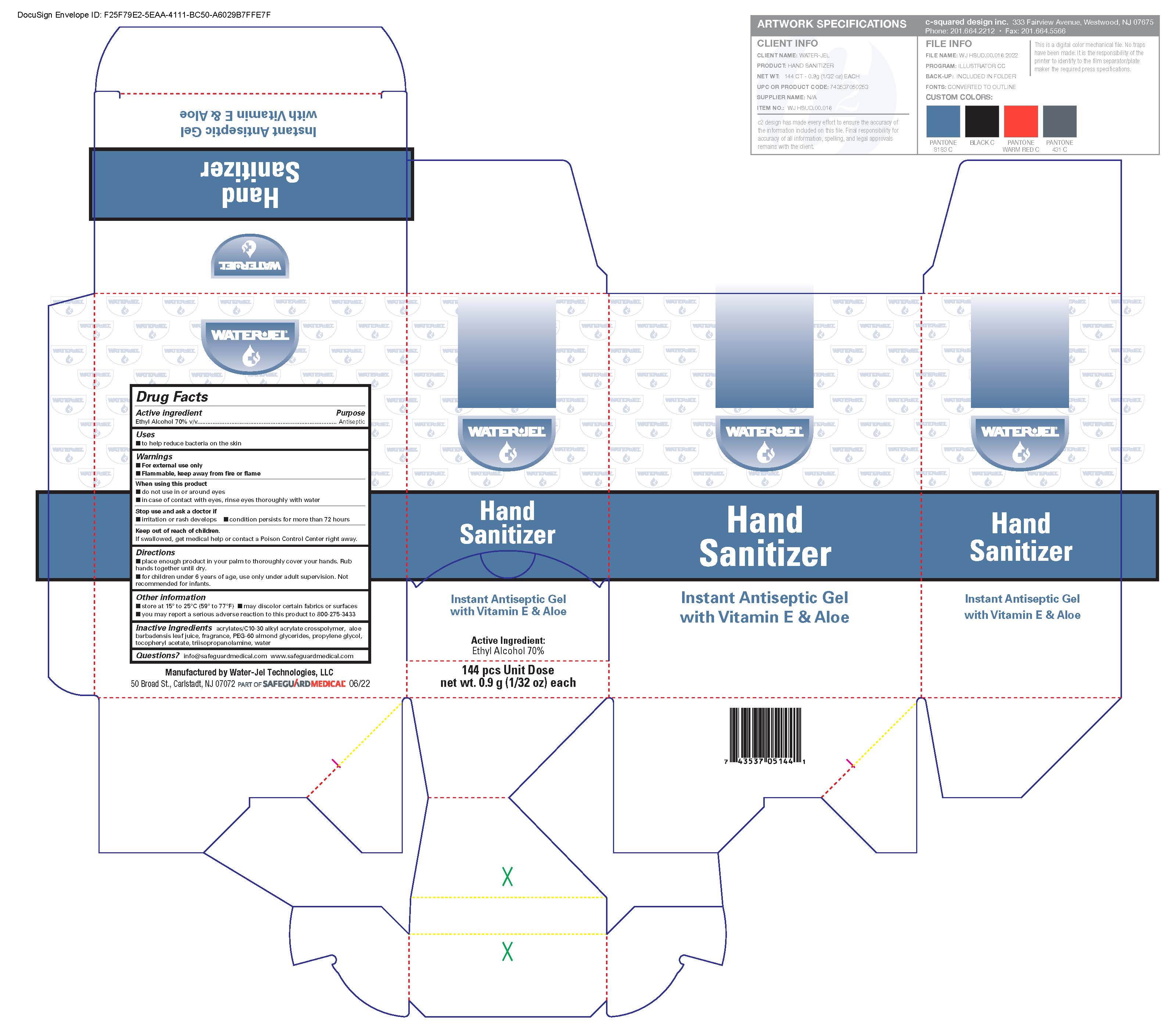 DRUG LABEL: Instant Hand Sanitizer
NDC: 59898-420 | Form: LIQUID
Manufacturer: Water-Jel Technologies
Category: otc | Type: HUMAN OTC DRUG LABEL
Date: 20250106

ACTIVE INGREDIENTS: ALCOHOL 62 mL/100 mL
INACTIVE INGREDIENTS: ALOE VERA LEAF; PROPYLENE GLYCOL; .ALPHA.-TOCOPHEROL ACETATE, DL-; TRIISOPROPANOLAMINE; CARBOMER COPOLYMER TYPE A; WATER

Instant Hand Sanitizer

Active ingredient

Ethyl alcohol 70% v/v

Purpose

Antiseptic

Uses

- to help reduce bacteria on the skin

Warnings

For external use only
Flammable, keep away from fire or flame

When using this product

- do not use in the eyes
- discontinue use if irritation and redness develops. If condition persists for more than 72 hours consult a doctor.

Keep out of reach of children

If swallowed, get medical help or contact a Poison Control Center right away.

- store at 15^0 to 25^0 C (59^0 to 77^0 F)
- may discolor certain fabrics or surfaces
- you may report a serious adverse reaction to this product to 800-275-3433

Inactive ingredients

acrylates/C10-30 alkyl acrylate crosspolymer, aloe barbadensis leaf juice, dl-alpha tocopheryl acetate, fragrance, PEG-60 almond glycerides, propylene glycol, tocopheryl acetate, purified water, triisopropanolamine

Questions

info@safeguardmedical.com www.safeguardmedical.com

Directions

- place enough product in your palm to thoroughly cover your hands. Rub hands together until dry.
- for children under 6 years of age, use only under adult supervision. Not recommended for infants.

Uses Directions

Uses

to help reduce bacteria on the skin

Directions

- place enough product in your palm to thoroughly cover your hands. Rub hands together until dry.
- for children under 6 years of age, use only under adult supervision. Not recommended for infants.

Principal Display Panel

Enter section text here